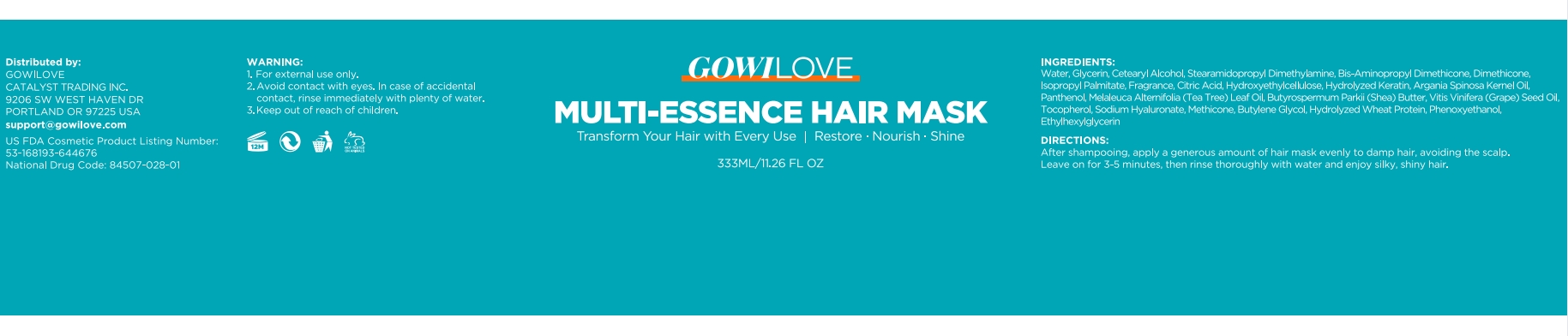 DRUG LABEL: GOWILOVE Multi-Essence Hair Mask
NDC: 84507-032 | Form: CREAM
Manufacturer: Guangdong Miaolian Cosmetics Co., Ltd.
Category: otc | Type: HUMAN OTC DRUG LABEL
Date: 20250226

ACTIVE INGREDIENTS: VITIS VINIFERA (GRAPE) SEED OIL 0.11 mg/100 mL; MELALEUCA ALTERNIFOLIA (TEA TREE) LEAF OIL 0.11 mg/100 mL; BUTYROSPERMUM PARKII (SHEA) BUTTER 0.11 mg/100 mL
INACTIVE INGREDIENTS: GLYCERIN; DIMETHICONE; HYDROLYZED WHEAT PROTEIN (ENZYMATIC, 3000 MW); WATER; FRAGRANCE 13576; TOCOPHEROL; CETEARYL ALCOHOL; STEARAMIDOPROPYL DIMETHYLAMINE; METHICONE (20 CST); CITRIC ACID; HYDROLYZED SHEEP WOOL KERATIN (200 MW); PANTHENOL; ARGANIA SPINOSA KERNEL OIL; PHENOXYETHANOL; BUTYLENE GLYCOL; HYDROXYETHYLCELLULOSE; SODIUM HYALURONATE; ISOPROPYL PALMITATE; ETHYLHEXYLGLYCERIN

DOSAGE AND ADMINISTRATION

After shampooing, apply an appropriate amount of conditioner to the hair gently massage - for 2-3 minutes, and then rinse off with clean water.

WARNINGS

Keep out of the reach of children. Avoid contact with the eyes. If you observe an unfavorable reaction, suspend use and, if it persists, consult a doctor.

INACTIVE INGREDIENT

WATER
GLYCERIN
CETEARYL ALCOHOL
STEARAMIDOPROPYL DIMETHYLAMINE
BIS-AMINOPROPYL DIMETHICONE
HYDROLYZED KERATIN
METHICONE
PHENOXYETHANOL
ETHYLHEXYLGLYCERIN
DIMETHICONE
ISOPROPYL PALMITATE
FRAGRANCE
CITRIC ACID
HYDROXYETHYLCELLULOSE
BUTYLENE GLYCOL
HYDROLYZED WHEAT PROTEIN
PANTHENOL
SODIUM HYALURONATE
ARGANIA SPINOSA KERNEL OIL
TOCOPHEROL

INDICATIONS AND USAGE

Deeply moisturizes hair. When used with Biotin Shampoo, it helps improve dryness, repair damage,and reduce split ends and breakage.

Keep out of the reach of children.

PURPOSE

Deeply moisturizes hair.

ACTIVE INGREDIENT

BUTYROSPERMUM PARKII (SHEA) BUTTER--------0.11%
MELALEUCA ALTERNIFOLIA (TEA TREE) LEAF OIL--------0.11%
VITIS VINIFERA (GRAPE) SEED OIL--------0.11%